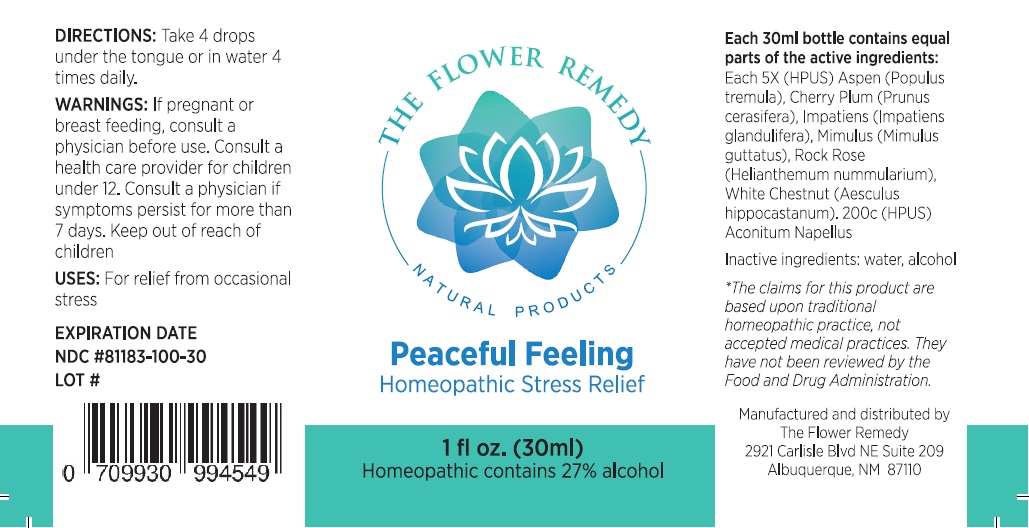 DRUG LABEL: THE FLOWER REMEDY Peaceful Feeling
NDC: 81183-100 | Form: LIQUID
Manufacturer: The Flower Remedy
Category: homeopathic | Type: HUMAN OTC DRUG LABEL
Date: 20251203

ACTIVE INGREDIENTS: IMPATIENS GLANDULIFERA FLOWER 5 [hp_X]/30 mL; HELIANTHEMUM NUMMULARIUM FLOWER 5 [hp_X]/30 mL; AESCULUS HIPPOCASTANUM FLOWER 5 [hp_X]/30 mL; PRUNUS CERASIFERA FLOWER 5 [hp_X]/30 mL; ERYTHRANTHE GUTTATA FLOWERING TOP 5 [hp_X]/30 mL; POPULUS TREMULA FLOWERING TOP 5 [hp_X]/30 mL; ACONITUM NAPELLUS WHOLE 200 [hp_C]/30 mL
INACTIVE INGREDIENTS: WATER; ALCOHOL

THE FLOWER REMEDY NATURAL PRODUCTS Peaceful Feeling

Active Ingredients:

Each 30ml bottle contains equal parts of the active ingredients:
Each 5X (HPUS) Aspen (Populus tremula), Cherry Plum (Prunus cerasifera), Impatiens (Impatiens glandulifera), Mimulus (Mimulus guttatus), Rock Rose (Helianthemum nummularium), White Chestnut (Aesculus hippocastanum). 200c (HPUS) Aconitum Napellus

Purpose:

Stress relief

USES:

For relief from occasional stress

DIRECTIONS:

Take 4 drops under the tongue or in water 4 times daily.

WARNINGS:

If pregnant or breast feeding, consult a physician before use. Consult a health care provider for children under 12. Consult a physician if symptoms persist for more than 7 days.

Keep out of reach of children.

Inactive ingredients:

water, alcohol

THE FLOWER REMEDY
NATURAL PRODUCTS

Homeopathic Stress Relief

Homeopathic contains 27% alcohol

*The claims for this product are based upon traditional homeopathic practice, not accepted medical practices. They have not been reviewed by the Food and Drug Administration.

Manufactured and distributed by
The Flower Remedy
2921 Carlisle Blvd NE Suite 209
Albuquerque, NM 87110